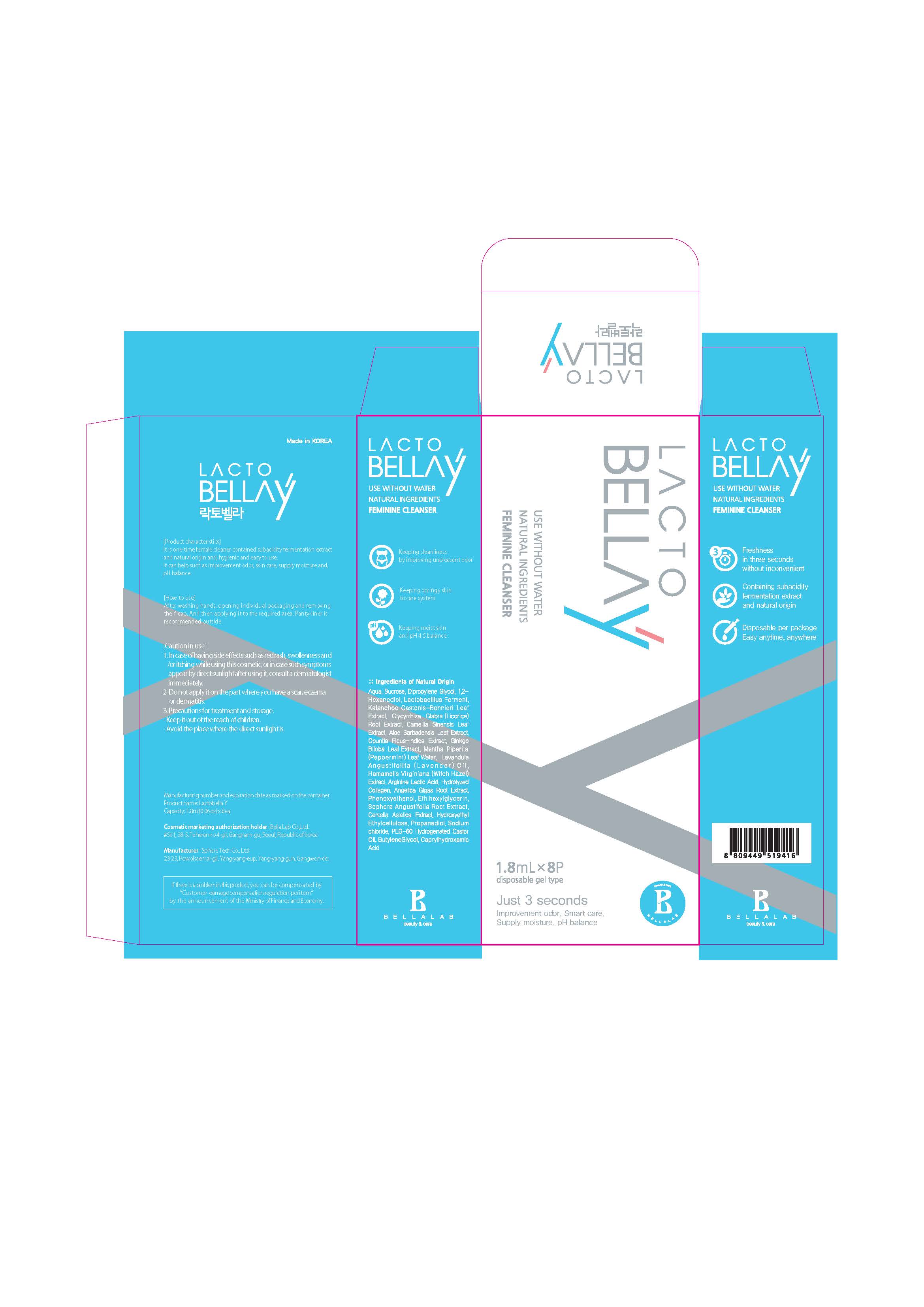 DRUG LABEL: LACTO BELLA Y
NDC: 72280-0001 | Form: GEL
Manufacturer: Bella Lab Co., Ltd.
Category: otc | Type: HUMAN OTC DRUG LABEL
Date: 20180427

ACTIVE INGREDIENTS: LACTOBACILLUS REUTERI 0.6 g/100 mL; SOPHORA FLAVESCENS ROOT 0.0015 g/100 mL; LAVENDER OIL 0.8 g/100 mL; SODIUM CHLORIDE 0.3 g/100 mL
INACTIVE INGREDIENTS: WATER

Drug Facts

ACTIVE INGREDIENT

Lactobacillus Ferment, Sophora Flavescens Root Extract, Lavandula Angustifolia (Lavender) Oil, Sodium Chloride

INACTIVE INGREDIENT

Water, etc.

PURPOSE

It is one-time female cleaner contained subacidity fermentation extract and natural origin and, hygienic and easy to use.
It can help such as improvement odor, skin care, supply moisture and, pH balance.

keep out of reach of the children

INDICATIONS AND USAGE

After washing hands, opening individual packaging and removing the Y cap.

And then applying it to the required area.

Panty-liner is recommended outside.

WARNINGS

1. In case of having side effects such as red rash, swollenness and /or itching while using this cosmetic, or in case such symptoms appear by direct sunlight after using it, consult a dermatologist immediately.
2. Do not apply it on the part where you have a scar, eczema or dermatitis.
3. Precautions for treatment and storage.
  - Keep it out of the reach of children.
  - Avoid the place where the direct sunlight is.

DOSAGE AND ADMINISTRATION

for external use only